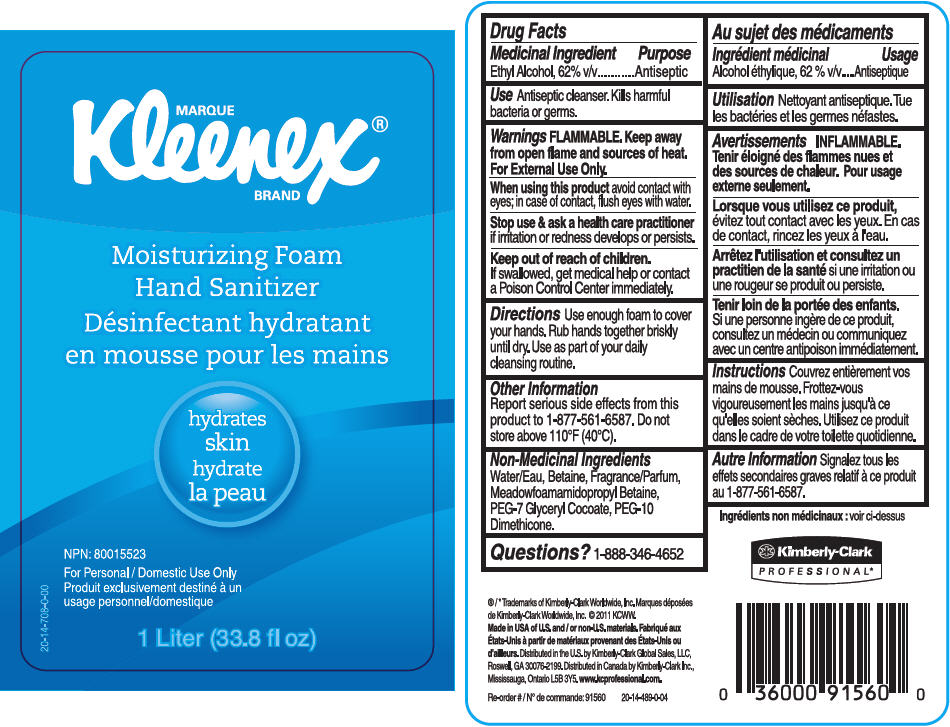 DRUG LABEL: Kleenex  Moisturizing Hand Sanitizer, Hydrates Skin
NDC: 55118-545 | Form: SOLUTION
Manufacturer: Kimberly-Clark Corporation
Category: otc | Type: HUMAN OTC DRUG LABEL
Date: 20141001

ACTIVE INGREDIENTS: Alcohol 62 mL/100 mL
INACTIVE INGREDIENTS: Water; Betaine; Peg-7 Glyceryl Cocoate

KLEENEX® Moisturizing Foam Hand Sanitizer

Drug Facts

Medicinal Ingredient

Ethyl Alcohol, 62% v/v

Purpose

Antiseptic

Use

Antiseptic cleanser. Kills harmful bacteria or germs.

Warnings

FLAMMABLE. Keep away from open flame and sources of heat.

For External Use Only.

When using this product avoid contact with eyes; in case of contact, flush eyes with water.

Stop use & ask a health care practitioner if irritation or redness develops or persists.

Keep out of reach of children. If swallowed, get medical help or contact a Poison Control Center immediately.

Directions

Use enough foam to cover your hands. Rub hands together briskly until dry. Use as part of your daily cleansing routine.

Other Information

Report serious side effects from this product to 1-877-561-6587. Do not store above 110°F (40°C).

Non-Medicinal Ingredients

Water/Eau, Betaine, Fragrance/Parfum, Meadowfoamamidopropyl Betaine, PEG-7 Glyceryl Cocoate, PEG-10 Dimethicone.

Questions?

1-888-346-4652

Distributed in the U.S. by Kimberly-Clark Global Sales, LLC,
Roswell, GA 30076-2199. Distributed in Canada by Kimberly-Clark Inc.,
Mississauga, Ontario L5B 3Y5.

PRINCIPAL DISPLAY PANEL - 1 Liter Container Label

MARQUE
Kleenex®
BRAND

Moisturizing Foam
Hand Sanitizer

hydrates
skin

NPN: 80015523

For Personal / Domestic Use Only

1 Liter (33.8 fl oz)

20-14-708-0-00